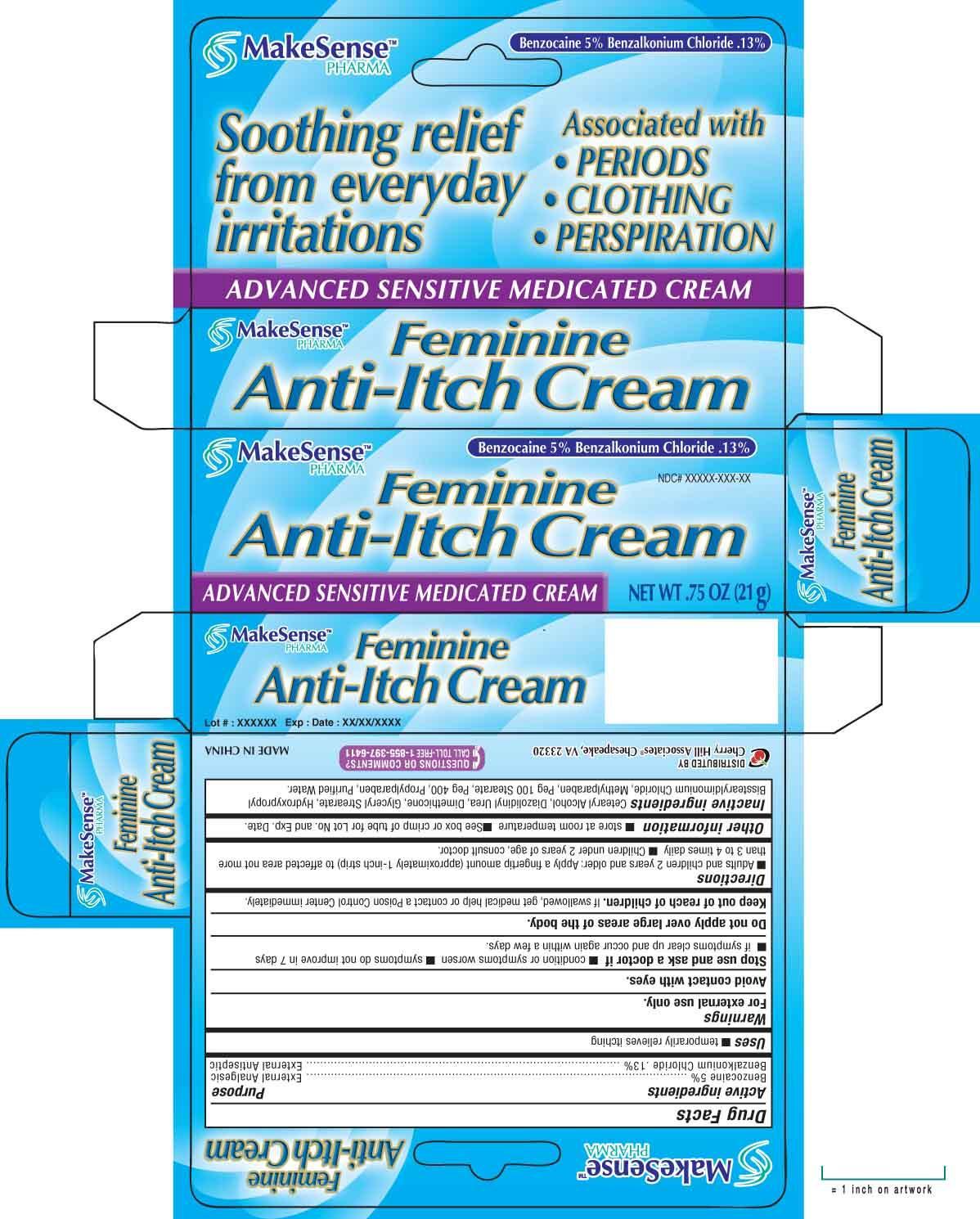 DRUG LABEL: MakeSense
NDC: 69020-209 | Form: CREAM
Manufacturer: Cherry Hill Sales Co
Category: otc | Type: HUMAN OTC DRUG LABEL
Date: 20140811

ACTIVE INGREDIENTS: BENZOCAINE 5 g/100 g; BENZALKONIUM CHLORIDE 130 mg/100 g
INACTIVE INGREDIENTS: CETOSTEARYL ALCOHOL; DIAZOLIDINYL UREA; DIMETHICONE; GLYCERYL MONOSTEARATE; HYDROXYPROPYL BISSTEARYLDIMONIUM CHLORIDE; METHYLPARABEN; PEG-100 STEARATE; POLYETHYLENE GLYCOL 400; PROPYLPARABEN; WATER

Drug Facts

Active Ingredients

Benzocaine 5%

Benzalkonium Chloride .13%

Purpose

External Analgesic

External Antiseptic

Uses

■ temporarily relieves itching

Warnings

For external use only

Avoid contact with eyes

Stop use and ask a doctor

■ condition or symptoms worsens ■ symptoms do not improve in 7 days ■ if symptoms clear up and occur again within a few days

Do not apply over large areas of the body

Keep out of reach of children

If swallowed, get medical help or contact a Poison Control Center right away

Directions

■ Adults and children 2 years of age and older: Apply a fingertip amount (approximately 1-inch strip) to affected area not more than 3 to 4 times daily ■ Children under 2 years of age: Consult a doctor

Inactive ingredients

Cetearyl Alcohol, Diaziolidinyl Urea, Dimethicone, Glyceryl Stearate, Hydroxpropyl Bisstearyldimonium Chloride, Methyparaben, Peg-100 Stearate, Peg-400, Propylparaben, Purified water